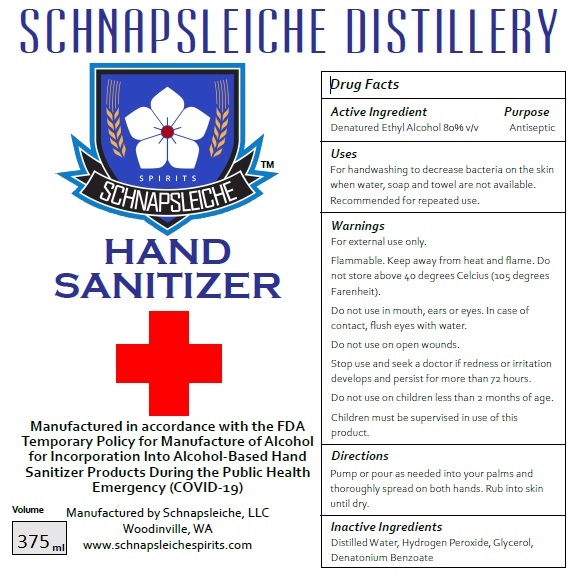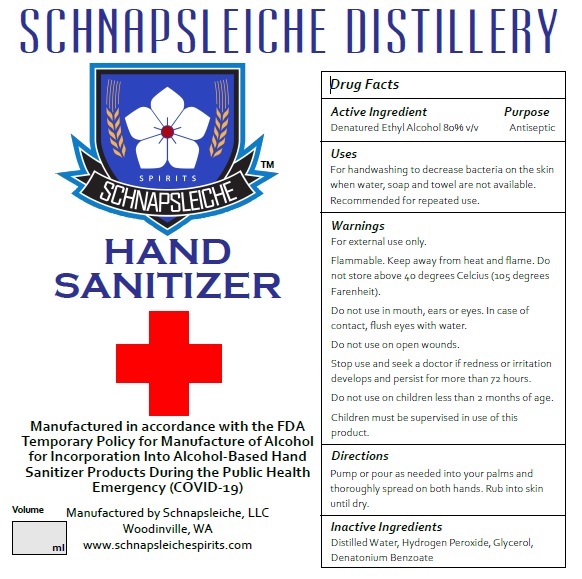 DRUG LABEL: Hand Sanitizer
NDC: 74852-0001 | Form: LIQUID
Manufacturer: Schnapsleiche LLC
Category: otc | Type: HUMAN OTC DRUG LABEL
Date: 20200408

ACTIVE INGREDIENTS: ALCOHOL 80 mL/100 mL
INACTIVE INGREDIENTS: GLYCERIN 1.45 mL/100 mL; HYDROGEN PEROXIDE 0.125 mL/100 mL; WATER

Hand Sanitizer

This is a hand sanitizer manufactured according to the Temporary Policy for Preparation of Certain Alcohol-Based Hand Sanitizer Products During the Public Health Emergency (CoViD-19); Guidance for Industry.

The hand sanitizer is manufactured using only the following United States Pharmacopoeia (USP) grade ingredients in the preparation of the product (percentage in final product formulation) consistent with World Health Organization (WHO) recommendations:

1. Alcohol (ethanol) (USP or Food Chemical Codex (FCC) grade) (80%, volume/volume (v/v)) in an aqueous solution denatured according to Alcohol and Tobacco Tax and Trade Bureau regulations in 27 CFR part 20.
2. Glycerol (1.45% v/v).
3. Hydrogen peroxide (0.125% v/v).
4. Sterile distilled water or boiled cold water.

The firm does not add other active or inactive ingredients. Different or additional ingredients may impact the quality and potency of the product.

Active Ingredient

Denatured Ethyl Alcohol 80% v/v

Purpose

Antiseptic

Use

For hand washing to help decrease bacteria on the skin when water, soap and towel are not available. Recommended for repeated use.

Warnings

For external use only.

Flammable. Keep away from heat or flame. Do not store above 40 degress Celcius (105 degrees Farenheit).

Do not use in mouth, ears or eyes. In ase of contact, flush eyes with water.

Do not use on open wounds.

Warnings
For external use only.
Flammable. Keep away from heat and flame. Do not store above 40 degrees Celcius (105 degrees Farenheit).
Do not use in mouth, ears or eyes. In case of contact, flush eyes with water.
Do not use on open wounds.
Stop use and seek a doctor if redness or irritation develops and persist for more than 72 hours.
Do not use on children less than 2 months of age.
Children must be supervised in use of this product.

Stop Use

Warnings
For external use only.
Flammable. Keep away from heat and flame. Do
not store above 40 degrees Celcius (105 degrees
Farenheit).
Do not use in mouth, ears or eyes. In case of
contact, flush eyes with water.
Do not use on open wounds.
Stop use and seek a doctor if redness or irritation
develops and persist for more than 72 hours.
Do not use on children less than 2 months of age.

Children must be supervised in use of this product.

Child Warning

Warnings
For external use only.
Flammable. Keep away from heat and flame. Do
not store above 40 degrees Celcius (105 degrees
Farenheit).
Do not use in mouth, ears or eyes. In case of
contact, flush eyes with water.
Do not use on open wounds.
Stop use and seek a doctor if redness or irritation
develops and persist for more than 72 hours.
Do not use on children less than 2 months of age.
Children must be supervised in use of this product.

Directions

Pump or pour as needed into your palms and thoroughly spread on both hands. Rub into skin until dry.

.

Other information

Warnings
For external use only.
Flammable. Keep away from heat and flame. Do not store above 40 degrees Celcius (105 degrees Farenheit).
Do not use in mouth, ears or eyes. In case of contact, flush eyes with water.
Do not use on open wounds.
Stop use and seek a doctor if redness or irritation develops and persist for more than 72 hours.
Do not use on children less than 2 months of age.
Children must be supervised in use of this product.

Inactive ingredients

Distilled Water, Hydrogen Peroxide, Glycerol,
Denatonium Benzoate

Package Label - Principal Display Panel

375 mL NDC: 74852-001-01

SCHNAPSLEICHE DISTILLERY

HAND SANITIZER

Manufactured in accordance with the FDA
Temporary Policy for Manufacture of Alcohol
for Incorporation Into Alcohol-Based Hand
Sanitizer Products During the Public Health
Emergency (COVID-19)

Volume 375ml

Manufactured by Schnapsleiche, LLC
Woodinville, WA
www.schnapsleichespirits.com